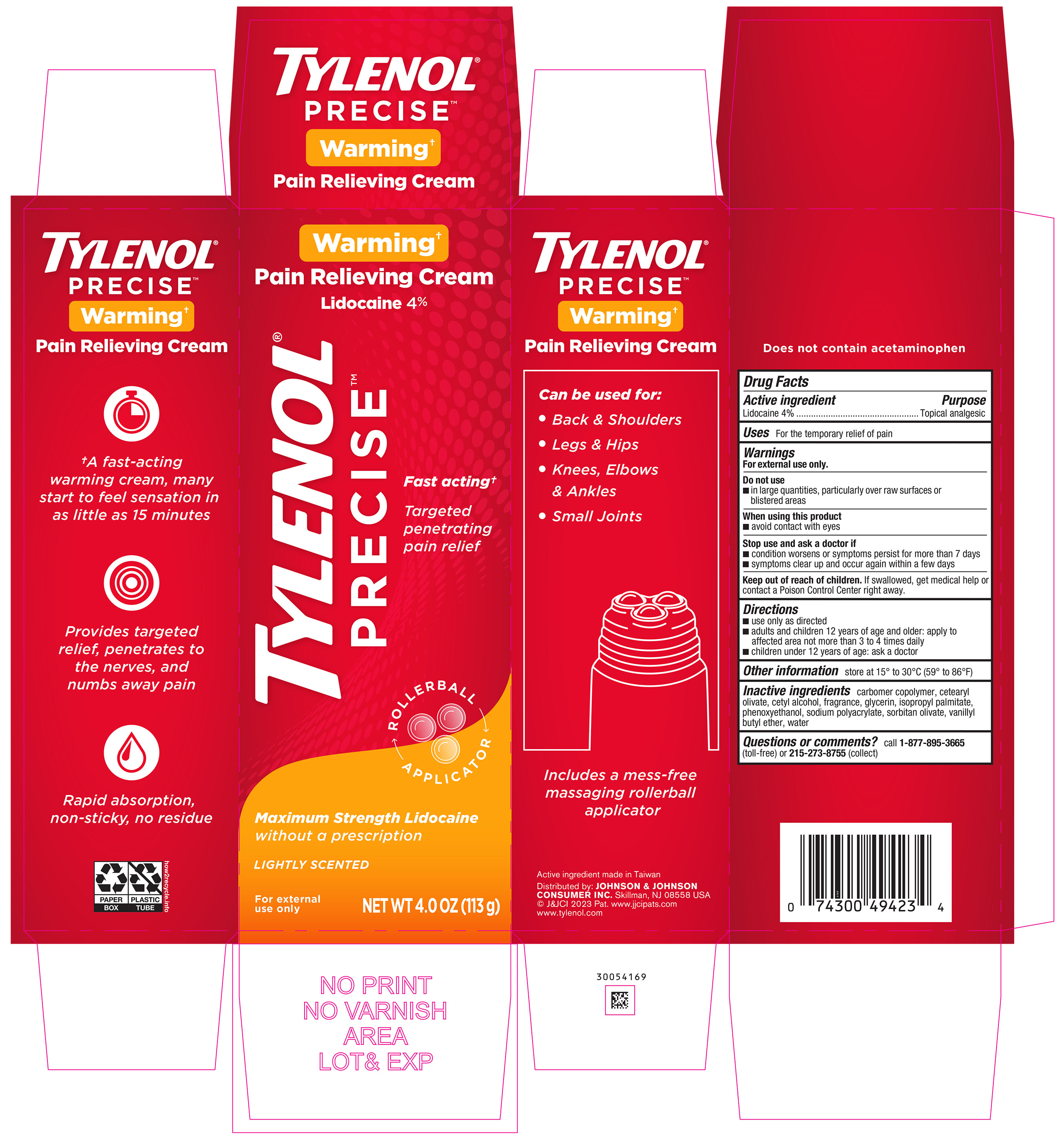 DRUG LABEL: Tylenol Precise Warming Pain Relieving
NDC: 69968-0794 | Form: CREAM
Manufacturer: Kenvue Brands LLC
Category: otc | Type: HUMAN OTC DRUG LABEL
Date: 20241113

ACTIVE INGREDIENTS: LIDOCAINE 40 mg/1 g
INACTIVE INGREDIENTS: CETEARYL OLIVATE; ISOPROPYL PALMITATE; PHENOXYETHANOL; VANILLYL BUTYL ETHER; CETYL ALCOHOL; WATER; GLYCERIN; CARBOMER INTERPOLYMER TYPE A (55000 CPS); SORBITAN OLIVATE

Tylenol Precise Warming Pain Relieving Cream

Drug Facts

ACTIVE INGREDIENT

Lidocaine 4%

PURPOSE

Topical analgesic

Uses

For the temporary relief of pain

Warnings

For external use only.

Do not use

- in large quantities, particularly over raw surfaces or blistered areas

When using this product

- avoid contact with eyes

Stop use and ask a doctor if

- condition worsens or symptoms persist for more than 7 days
- symptoms clear up and occur again within a few days

Keep out of reach of children. If swallowed, get medical help or contact a Poison Control Center right away.

Directions

- use only as directed
- adults and children 12 years of age and older: apply to affected area not more than 3 to 4 times daily
- children under 12 years of age: ask a doctor

Other Information

store at 15^0 to 30^0 C (59^0 to 86^0 F)

Inactive Ingredients

carbomer copolymer, cetearyl olivate, cetyl alcohol, fragrance, glycerin, isopropyl palmitate, phenoxyethanol, sodium polyacrylate, sorbitan olivate, vanillyl butyl ether, water

Questions?

Call 1-877-895-3665 (toll-free) or 215- 273-8755 (collect)

Distributed by:
JOHNSON & JOHNSON CONSUMER INC.
Skillman, NJ 08558 USA

PRINCIPAL DISPLAY PANEL - 113 g Tube Carton

Warming†

Pain Relieving Cream

Lidocaine 4%

TYLENOL®

PRECISETM

Fast acting†

Targeted

penetrating

pain relief

ROLLER BALL

APPLICATOR

Maximum Strength Lidocaine

without a prescription

LIGHTLY SCENTED

For external

use only

NET WT 4.0 OZ (113 g)